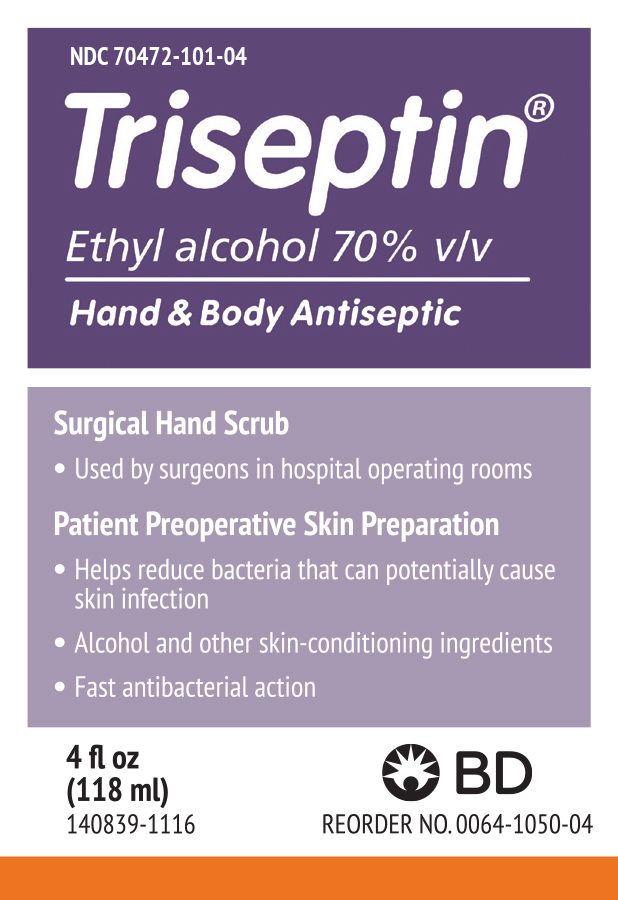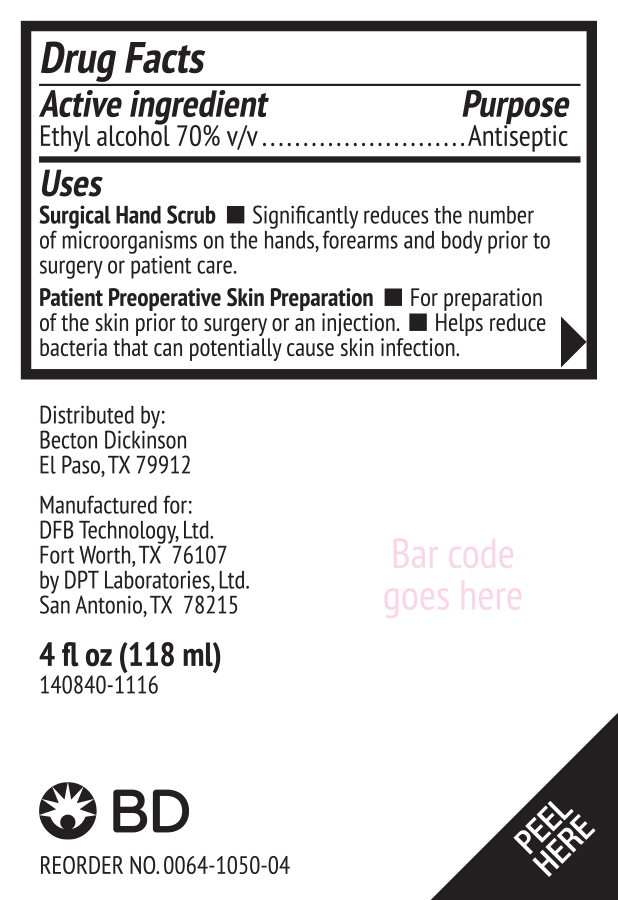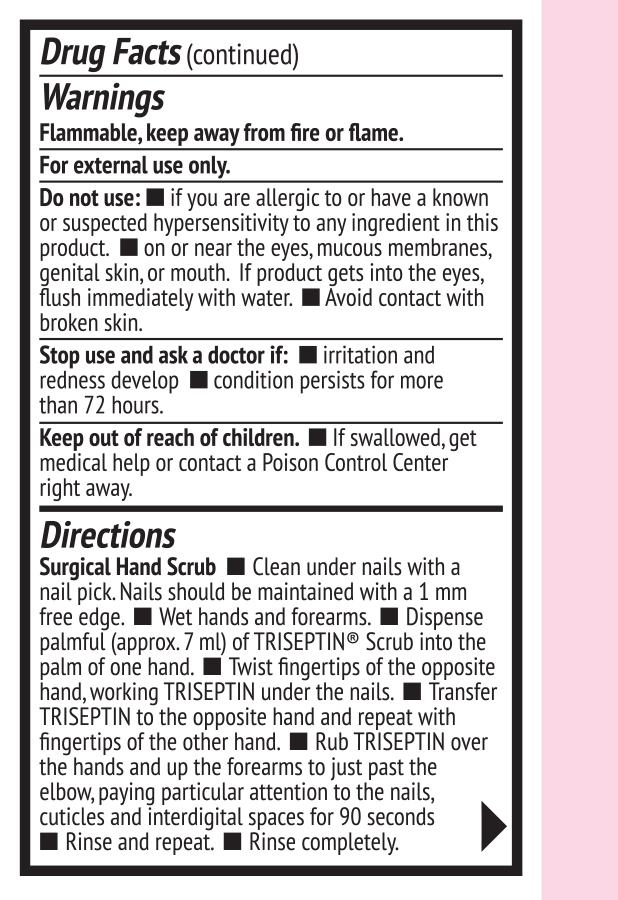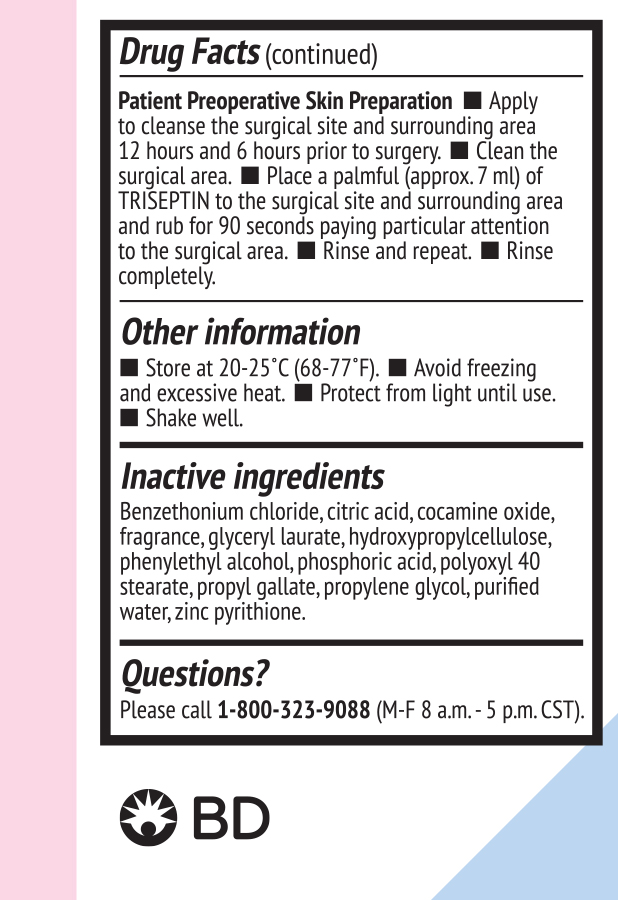 DRUG LABEL: TRISEPTIN
NDC: 70472-101 | Form: LOTION
Manufacturer: DFB Technology Ltd
Category: otc | Type: HUMAN OTC DRUG LABEL
Date: 20171230

ACTIVE INGREDIENTS: ALCOHOL 0.7 mL/1 mL
INACTIVE INGREDIENTS: BENZETHONIUM CHLORIDE; CITRIC ACID MONOHYDRATE; COCAMINE OXIDE; GLYCERYL LAURATE; HYDROXYPROPYL CELLULOSE; PHENYLETHYL ALCOHOL; PHOSPHORIC ACID; POLYOXYL 40 STEARATE; PROPYL GALLATE; PROPYLENE GLYCOL; WATER; PYRITHIONE ZINC

TRISEPTIN Hand and Body Antiseptic

Drug Facts

Active Ingredient

Ethyl Alcohol 70% v/v

Purpose

Antiseptic

Uses

Surgical Hand Scrub

- Significantly reduces the number of microorganisms on the hands, forearms and body prior to surgery or patient care.

Patient Preoperative Skin Preparation

- For preparation of the skin prior to surgery or an injection.
- Helps reduce bacteria that can potentially cause skin infection.

Warnings

Flammable, keep away from fire or flame.
For external use only.

Do not Use:

- if you are allergic to or have a known or suspected hypersensitivity to any ingredient in this product.
- on or near the eyes, mucous membranes, genital skin, or mouth. If product gets into the eyes, flush immediately with water.
- Avoid contact with broken skin.

Stop use and ask a doctor if:

- irritation and redness develop
- condition persists for more than 72 hours

Keep out of reach of chipdren.

If swallowed, get medical help or contact a Poison Control Center right away.

Directions

Surgical Hand Scrub

- Clean under nails with a nail pick. Nails should be maintained with a 1 mm free edge.
- Wet hands and forearms.
- Dispense palmful (approx. 7 ml) of TRISEPTIN® Scrub into the palm of one hand.
- Twist fingertips of the opposite hand, working TRISEPTIN under the nails.
- Transfer TRISEPTIN to the opposite hand and repeat with fingertips of the other hand.
- Rub TRISEPTIN over the hands and up the forearms to just past the elbow, paying particular attention to the nails, cuticles and interdigital spaces for 90 seconds.
- Rinse and repeat.
- Rinse completely.

Patient Preoperative Skin Preparation

- Apply to cleanse the surgical site and surrounding area 12 hours and 6 hours prior to surgery.
- Clean the surgical area.
- Place a palmful (approx. 7 ml) of TRISEPTIN to the surgical site and surrounding area and rub for 90 seconds paying particular attention to the surgical area.
- Rinse and repeat.
- Rinse completely.

Other information

- Store upright at 20-25°C (68-77°F).
- Avoid freezing and excessive heat.
- Protect from light until use.
- Shake well.

Inactive ingredients

Benzethonium chloride, citric acid, cocamine oxide, fragrance, glyceryl laurate, hydroxypropylcellulose, phenylethyl alcohol, phosphoric acid, polyoxyl 40 stearate, propyl gallate, propylene glycol, purified water, zinc pyrithione.

Questions?

Please call 1-800-323-9088 (M-F 8 a.m. - 5 p.m. CST).

Distributed by:
Becton Dickinson
El Paso, TX 79912
Manufactured for:
DFB Technology, Ltd.
Fort Worth, TX 76107
by DPT Laboratories, Ltd.
San Antonio, TX 78215
4 fl oz (118 mL)
140840-1116

PRINCIPAL DISPLAY PANEL

NDC 70472-101-04
Triseptin®
Ethyl alcohol 70% v/v
Hand & Body Antiseptic

Surgical Hand Scrub

- Used by surgeons in hospital operating rooms

Patient Preoperative Skin Preparation

- Helps reduce bacteria that can potentially cause skin infection
- Alcohol and other skin-conditioning ingredients
- Fast antibacterial action

4 fl oz
(118 ml)
140839-1116

BD
REORDER NO. 0064-1050-04

PACKAGE LABEL.PRINCIPAL DISPLAY PANEL